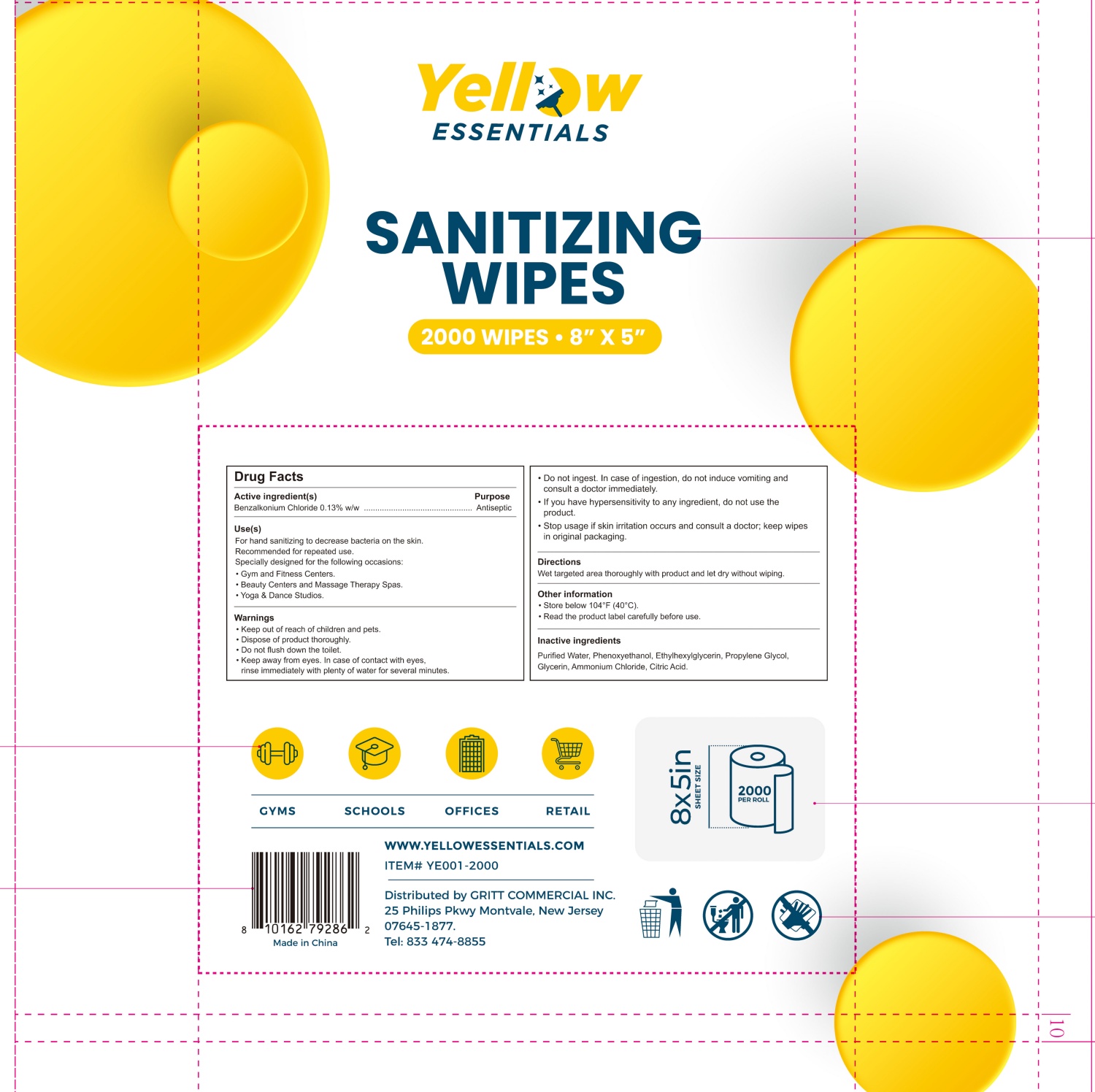 DRUG LABEL: YELLOW ESSENTIALS SANITIZING WIPES
NDC: 87039-001 | Form: CLOTH
Manufacturer: Gritt Commercial Inc.
Category: otc | Type: HUMAN OTC DRUG LABEL
Date: 20251225

ACTIVE INGREDIENTS: BENZALKONIUM CHLORIDE 0.13 g/100 g
INACTIVE INGREDIENTS: AMMONIUM CHLORIDE; ETHYLHEXYLGLYCERIN; CITRIC ACID; WATER; PHENOXYETHANOL; GLYCERIN; PROPYLENE GLYCOL

87039-001 YELLOW ESSENTIALS SANITIZING WIPES

Active ingredient(s)

Benzalkonium Chloride 0.13% w/w

Purpose

Antiseptic

INDICATIONS AND USAGE

Use(s)

For hand sanitizing to decrease bacteria on the skin.

Recommended for repeated use.

Specially designed for the following occasions:

· Gym and Fitness Centers.

· Beauty Centers and Massage Therapy Spas.

· Yoga & Dance Studios.

Warnings

· Keep out of reach of children and pets.

· Dispose of product thoroughly.

· Do not flush down the toilet.

· Keep away from eyes. In case of contact with eyes,

rinse immediately with plenty of water for several minutes.

· Do not ingest. In case of ingestion, do not induce vomiting and

consult a doctor immediately.

· If you have hypersensitivity to any ingredient, do not use the

product.

· Stop usage if skin irritation occurs and consult a doctor; keep wipes

in original packaging.

· Keep out of reach of children and pets.

Directions

Wet targeted area thoroughly with product and let dry without wiping.

Inactive ingredients

Purified Water, Phenoxyethanol, Ethylhexylglycerin, Propylene Glycol,

Glycerin, Ammonium Chloride, Citric Acid.

PACKAGE LABEL

Yellow

ESSENTIALS

SANITIZING

WIPES

2000 WIPES · 8″ × 5″

NDC: 87039-001-01